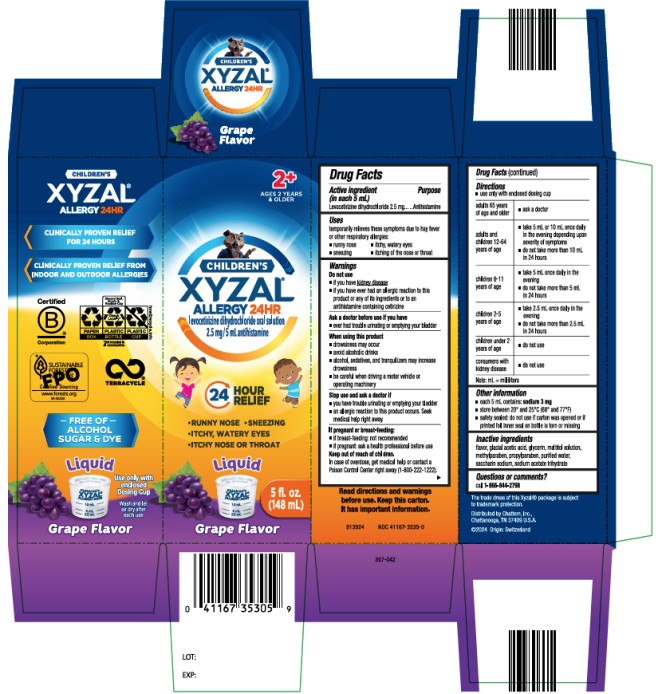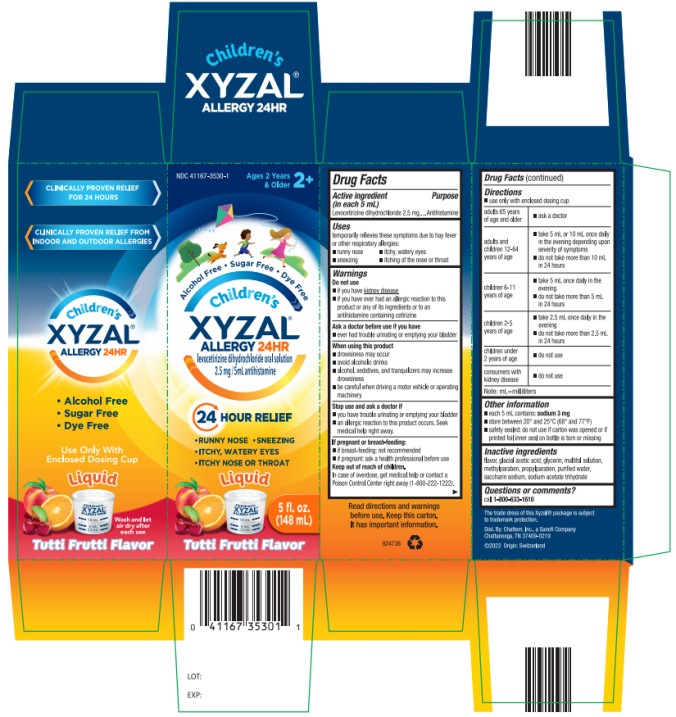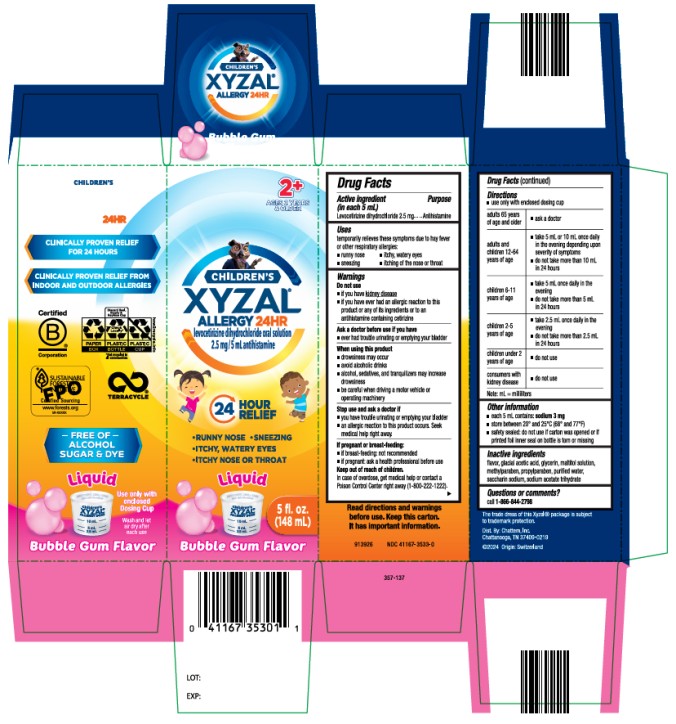 DRUG LABEL: Childrens Xyzal Allergy
NDC: 41167-3535 | Form: SOLUTION
Manufacturer: Chattem, Inc.
Category: otc | Type: HUMAN OTC DRUG LABEL
Date: 20260121

ACTIVE INGREDIENTS: LEVOCETIRIZINE DIHYDROCHLORIDE 2.5 mg/5 mL
INACTIVE INGREDIENTS: ACETIC ACID; GLYCERIN; MALTITOL; METHYLPARABEN; PROPYLPARABEN; WATER; SACCHARIN SODIUM; SODIUM ACETATE

Childrens Xyzal Allergy

Children’s Xyzal® Allergy 24HR

Drug Facts

Active ingredient (in each 5 mL)

Levocetirizine dihydrochloride 2.5 mg

Purpose

Antihistamine

Uses

temporarily relieves these symptoms due to hay fever or other respiratory allergies:

■ runny nose ■ sneezing ■ itchy, watery eyes ■ itching of the nose or throat

Warnings

Do not use

■ if you have kidney disease

■ if you have ever had an allergic reaction to this product or any of its ingredients or to an antihistamine containing cetirizine

Ask a doctor before use if you have

■ ever had trouble urinating or emptying your bladder

When using this product

■ drowsiness may occur

■ avoid alcoholic drinks

■ alcohol, sedatives, and tranquilizers may increase drowsiness

■ be careful when driving a motor vehicle or operating machinery

Stop use and ask a doctor if

■ you have trouble urinating or emptying your bladder

■ an allergic reaction to this product occurs. Seek medical help right away.

If pregnant or breast-feeding:

■ if breast-feeding: not recommended

■ if pregnant: ask a health professional before use

Keep out of reach of children.

In case of overdose, get medical help or contact a Poison Control Center right away (1-800-222-1222).

Directions

■ use only with enclosed dosing cup

adults 65 years of age and older | ■ ask a doctor
adults and children 12-64 years of age | ■ take 5 mL or 10 mL once daily in the evening depending upon severity of symptoms ■ do not take more than 10 mL in 24 hours
children 6-11 years of age | ■ take 5 mL once daily in the evening ■ do not take more than 5 mL in 24 hours
children 2-5 years of age | ■ take 2.5 mL once daily in the evening ■ do not take more than 2.5 mL in 24 hours
children under 2 years of age | ■ do not use
consumers with kidney disease | ■ do not use
Note: mL=milliliters

Other information

■ each 5 mL contains: sodium 3 mg

■ store between 20° and 25°C (68° and 77°F)

■ safety sealed: do not use if carton was opened or if printed foil inner seal on bottle is torn or missing

Inactive ingredients

flavor, glacial acetic acid, glycerin, maltitol solution, methylparaben, propylparaben, purified water, saccharin sodium, sodium acetate trihydrate

Questions or comments?

call 1-866-844-2798

PRINCIPAL DISPLAY PANEL

Children’s Xyzal
Allergy 24HR
Liquid
Grape Flavor

PRINCIPAL DISPLAY PANEL

Children’s Xyzal
Allergy 24HR
Liquid
Tutti Frutti Flavor

PRINCIPAL DISPLAY PANEL

Children’s Xyzal
Allergy 24HR
Liquid
Bubble Gum Flavor